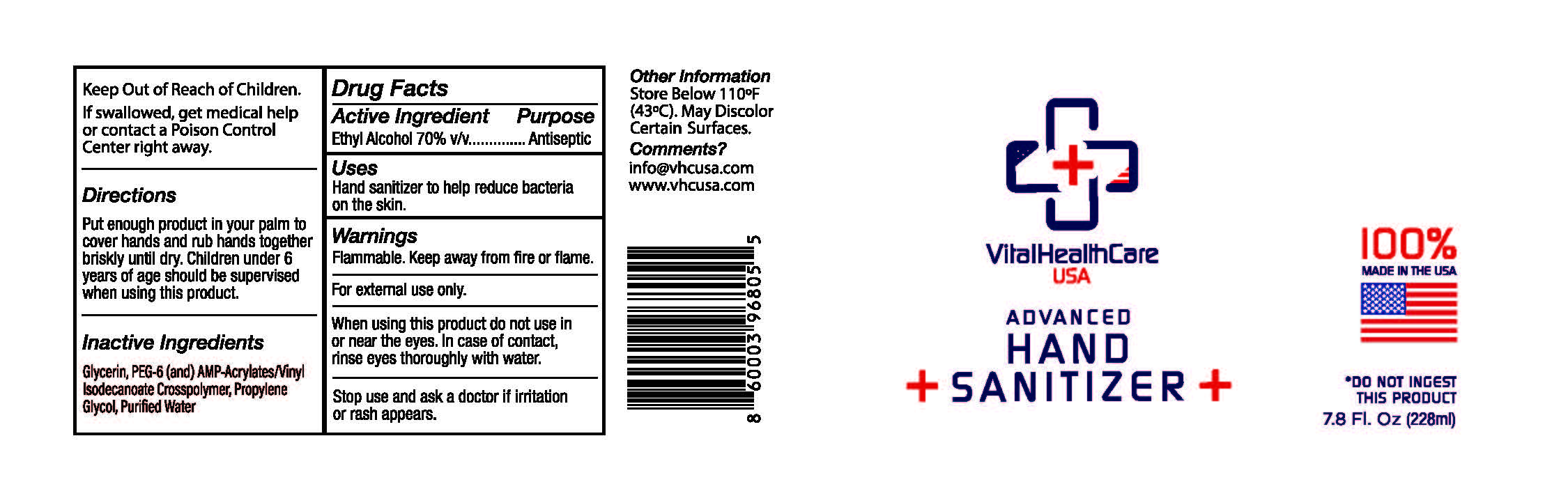 DRUG LABEL: Vital Health Care Advanced Hand Sanitizer
NDC: 73787-127 | Form: GEL
Manufacturer: FGD, LLC
Category: otc | Type: HUMAN OTC DRUG LABEL
Date: 20210106

ACTIVE INGREDIENTS: ALCOHOL 70 mL/100 mL
INACTIVE INGREDIENTS: ACRYLATES/VINYL ISODECANOATE CROSSPOLYMER (10000 MPA.S NEUTRALIZED AT 0.5%); WATER; PROPYLENE GLYCOL; GLYCERIN; POLYETHYLENE GLYCOL 300

Vital Health Care Advanced Hand Sanitizer 7.8 oz

Active ingredient

Ethyl Alcohol 70%

PURPOSE

Antiseptic

Uses

Hand sanitizer to help reduce bacteria on the skin.

Warnings

For external use only. Flammable. Keep away from heat or flame.

DO NOT USE

- on children less than 2 months of age
- on open skin wounds

WHEN USING

keep out of eyes, ears, and mouth. In case of contact with eyes, rinse eyes thoroughly with water.

STOP USE

if irritation or rash occurs. These may be signs of a serious condition.

KEEP OUT OF REACH OF CHILDREN

If swallowed, get medical help or contact a Poison Control Center right away.

Directions

- Put enough product in your palm to cover hands and rub hands together briskly until dry.
- Children under 6 years of age should be supervised when using this product.

OTHER SAFETY INFORMATION

- Store between 15-30oC (59-86oF)
- Avoid freezing and excessive heat 40oC (104oF)

Inactive ingredients

Glycerin, PEG-6 (and) AMP-Acrylate/vinyl-Isodecanoate Crosspolymer, Propylene-glycol, Purified Water